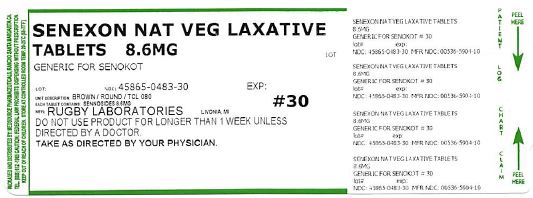 DRUG LABEL: SENEXON
NDC: 45865-483 | Form: TABLET, COATED
Manufacturer: Medsource Pharmaceuticals
Category: otc | Type: HUMAN OTC DRUG LABEL
Date: 20180721

ACTIVE INGREDIENTS: SENNOSIDES A AND B 8.6 mg/1 1
INACTIVE INGREDIENTS: CROSCARMELLOSE SODIUM; DIBASIC CALCIUM PHOSPHATE DIHYDRATE; HYPROMELLOSE 2910 (6 MPA.S); MAGNESIUM STEARATE; CELLULOSE, MICROCRYSTALLINE	; MINERAL OIL

Active ingredient (in each tablet) Sennosides 8.6mg

Ask a doctor or pharmacist before use if you are taking any other drug. Take this product tow or more hours before or after other drugs. Laxatives may affect how other drugs work.

Ask a doctor before use if you have noticed a sudden change in bowel habits that lasts over two weeks.

Do not use for longer than one week, when abdominal pain, nausea or vomiting are present.

Stop use and ask a doctor if: you have rectal bleeding; you fail to have a bowel movement after use of this product. These may indicate a serious condition.

PREGNANCY OR BREAST FEEDING

If pregnant or breast-feeding, ask a health professional before use.

uses

relieves occasional constipation(irregularity);generally causes bowel movement in 6-12 hours.

QUESTIONS

1800 645-2158 9 am - 5 pm Monday - Friday

Keep out of reach of children. In case of overdose, get medical help or contact a Poison Control Center right away.

INACTIVE INGREDIENT

Inactive Ingredients croscarmellose sodium, dibasic calcium phosphate dihydrate, hypromellose, magnesium stearate, microcrystalline cellulose, minerol oil

Dosage and Administration

Adults and children 12 years and over - 2 tablets once a day - maximum dosage - 4 tablets twice a day

Children 6 to under 12 years - 1 tablet once a day maximum dosage - 2 tablets twice a day

children 2 to under 6 years - 1/2 tablet once a day - maximum dosage - 1 tablet twice a day

INDICATIONS AND USAGE

Relieves occasional constipation

Generally produces bowel movement in 6-12 hours